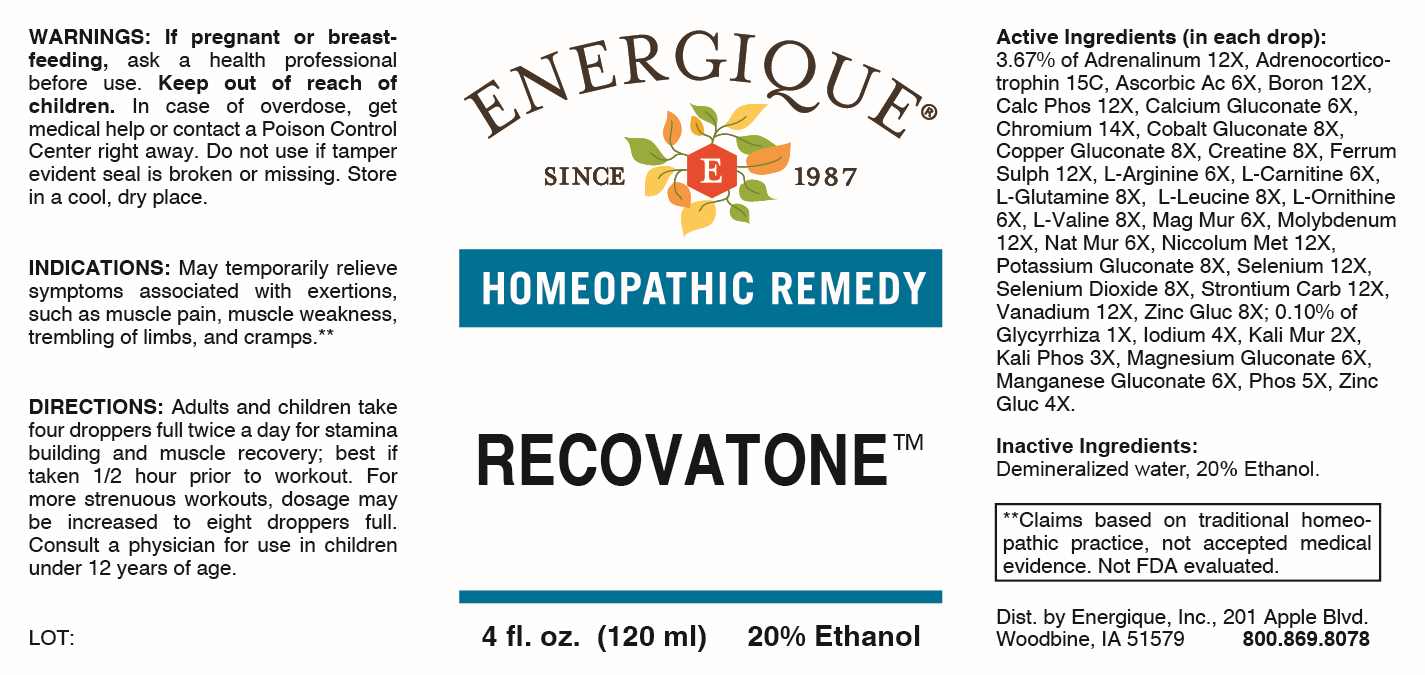 DRUG LABEL: Recovatone
NDC: 44911-0734 | Form: LIQUID
Manufacturer: Energique, Inc.
Category: homeopathic | Type: HUMAN OTC DRUG LABEL
Date: 20250128

ACTIVE INGREDIENTS: GLYCYRRHIZA GLABRA 1 [hp_X]/1 mL; POTASSIUM CHLORIDE 2 [hp_X]/1 mL; DIBASIC POTASSIUM PHOSPHATE 3 [hp_X]/1 mL; IODINE 4 [hp_X]/1 mL; ZINC GLUCONATE 4 [hp_X]/1 mL; PHOSPHORUS 5 [hp_X]/1 mL; ASCORBIC ACID 6 [hp_X]/1 mL; CALCIUM GLUCONATE 6 [hp_X]/1 mL; ARGININE 6 [hp_X]/1 mL; LEVOCARNITINE 6 [hp_X]/1 mL; ORNITHINE 6 [hp_X]/1 mL; MAGNESIUM CHLORIDE 6 [hp_X]/1 mL; MAGNESIUM GLUCONATE 6 [hp_X]/1 mL; MANGANESE GLUCONATE 6 [hp_X]/1 mL; SODIUM CHLORIDE 6 [hp_X]/1 mL; COBALTOUS GLUCONATE 8 cm2/1 mL; COPPER GLUCONATE 8 [hp_X]/1 mL; CREATINE 8 [hp_X]/1 mL; GLUTAMINE 8 [hp_X]/1 mL; LEUCINE 8 [hp_X]/1 mL; VALINE 8 [hp_X]/1 mL; POTASSIUM GLUCONATE 8 [hp_X]/1 mL; SELENIUM DIOXIDE 12 [hp_X]/1 mL; EPINEPHRINE 12 [hp_X]/1 mL; BORON 12 [hp_X]/1 mL; TRIBASIC CALCIUM PHOSPHATE 12 [hp_X]/1 mL; FERROUS SULFATE 12 [hp_X]/1 mL; MOLYBDENUM 12 [hp_X]/1 mL; NICKEL 12 [hp_X]/1 mL; SELENIUM 12 [hp_X]/1 mL; STRONTIUM CARBONATE 12 [hp_X]/1 mL; VANADIUM 12 [hp_X]/1 mL; CHROMIUM 14 [hp_X]/1 mL; CORTICOTROPIN 15 [hp_C]/1 mL
INACTIVE INGREDIENTS: WATER; ALCOHOL

DRUG FACTS:

ACTIVE INGREDIENTS:

(in each drop): 3.67% of Adrenalinum 12X, Adrenocorticotrophin 15C, Ascorbicum Acidum 6X, Boron 12X, Calcarea Phosphorica 12X, Calcium Gluconate 6X, Chromium 14X, Cobalt Gluconate 8X, Copper Gluconate 8X, Creatine 8X, Ferrous Sulphuricum 12X, L-Arginine 6X, L-Carnitine 6X, L-Glutamine 8X, L-Leucine 8X, L-Ornithine 6X, L-Valine 8X, Magnesia Muriatica 6X, Molybdenum 12X, Natrum Muriaticum 6X, Niccolum Metallicum 12X, Potassium Gluconate 8X, Selenium Metallicum 12X, Selenium Dioxide 8X, Strontium Carbonicum 12X, Vanadium Metallicum 12X, Zincum Gluconicum 8X; 0.10% of Glycyrrhiza Glabra 1X, Iodium 4X, Kali Muriaticum 2X, Kali Phosphoricum 3X, Magnesium Gluconicum Dihydricum 6X, Manganese Gluconate 6X, Phosphorus 5X, Zincum Gluconicum 4X.

PURPOSE:

May temporarily relieve symptoms associated with exertions, such as muscle pain, muscle weakness, trembling of limbs, and cramps.**

**Claims based on traditional homeopathic practice, not accepted medical evidence. Not FDA evaluated.

WARNINGS:

If pregnant or breast-feeding, ask a health professional before use.

Keep out of reach of children. In case of overdose, get medical help or contact a Poison Control Center right away.

Do not use if tamper evident seal is broken or missing.

Store in a cool, dry place.

KEEP OUT OF REACH OF CHILDREN:

In case of overdose, get medical help or contact a Poison Control Center right away.

DIRECTIONS:

Adults and children take four droppers full twice a day for stamina building and muscle recovery; best if taken 1/2 hour prior to workout. For more strenuous workouts, dosage may be increased to eight droppers full.

Consult a physician for use in children under 12 years of age.

INDICATIONS:

May temporarily relieve symptoms associated with exertions, such as muscle pain, muscle weakness, trembling of limbs, and cramps.**

**Claims based on traditional homeopathic practice, not accepted medical evidence. Not FDA evaluated.

INACTIVE INGREDIENTS:

Demineralized water, 20% Ethanol.

QUESTIONS:

Dist. by Energique, Inc.,

201 Apple Blvd.
Woodbine, IA 51579

800.869.8078

PACKAGE LABEL DISPLAY:

ENERGIQUE

SINCE 1987

HOMEOPATHIC REMEDY

RECOVATONE

4 fl. oz. (120 ml)